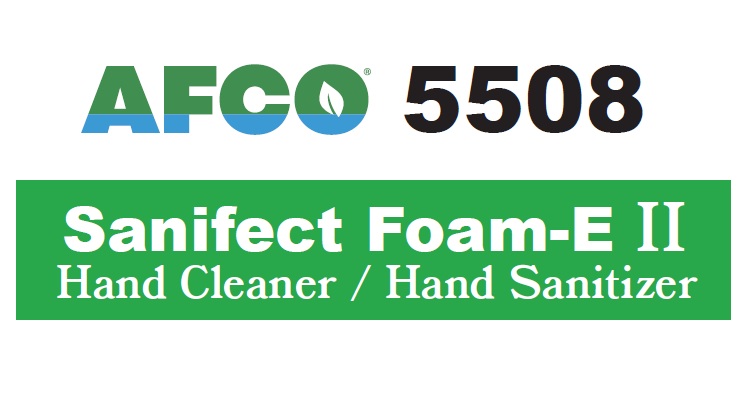 DRUG LABEL: AFCO 5508 Sanifect Foam-E II
NDC: 66949-139 | Form: LIQUID
Manufacturer: Zep Inc.
Category: otc | Type: HUMAN OTC DRUG LABEL
Date: 20251226

ACTIVE INGREDIENTS: CHLOROXYLENOL 2081980 mg/208198 mL
INACTIVE INGREDIENTS: AMMONIUM LAURETH-2 SULFATE; WATER; AMMONIUM LAURYL SULFATE; PROPYLENE GLYCOL; GLYCERIN; EDETATE DISODIUM; ALCOHOL; COCAMIDE MEA

66949-139 / AF5508 AFCO Sanifect Foam-E II

Active ingredient

Chloroxylenol 1.0% w/w

Purpose

Antiseptic

Uses

- Hand wash to help reduce bacteria on skin that potentially can cause diseases.
- Helps prevent cross contamination by hand contact.
- Recommended for repeat use.

Warnings

For external use only – Harmful if swallowed.

When using this product do not use in or near eyes. If eye contact occurs, rinse eyes thoroughly with water. Discontinue use if irritation or redness develops.

Stop use and ask a doctor if skin irritation or redness persists for more than 72 hours.

Keep out of reach of children. In case of accidental ingestion, seek medical attention or contact poison control center immediately.

Directions

- For one step hand washing and sanitizing, wet hands with water.
- Apply a generous amount of product in palm of hand and work into later.
- Rinse thoroughly with potable water.
- Dry hands completely.

Other information

For Food Processing, Food Service and Professional Use Only.

Inactive ingredients

Water, Ammonium Lauryl Sulfate, Ammonium Laureth Sulfate, Ethyl Alcohol, Propylene Glycol, Cocamide MEA, Glycerin, Disodium EDTA.

Questions or comments?

For product or technical information, contact ZEP, INC. Monday to Friday 8 AM to 4 PM EST at 1-877-428-9937 or visit our website at www.zep.com.